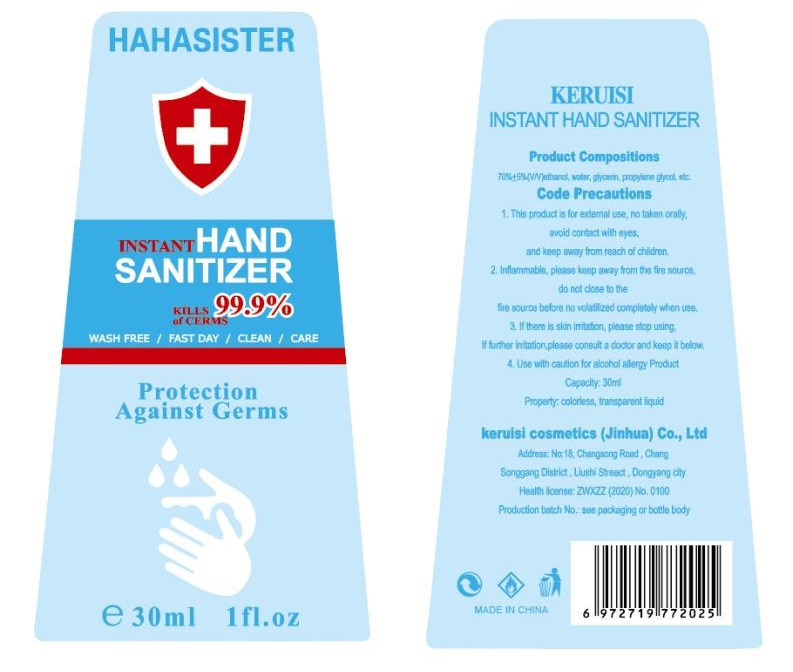 DRUG LABEL: Instant Hand Sanitizer
NDC: 55422-001 | Form: LIQUID
Manufacturer: KeRuiSi Cosmetics (Jinhua) Co.,Ltd.
Category: otc | Type: HUMAN OTC DRUG LABEL
Date: 20200512

ACTIVE INGREDIENTS: ALCOHOL 22.5 mL/30 mL
INACTIVE INGREDIENTS: PROPYLENE GLYCOL; AMINOMETHYLPROPANOL; CARBOMER HOMOPOLYMER, UNSPECIFIED TYPE; GLYCERIN; WATER

DOSAGE AND ADMINISTRATION

Store in a cool dry place.

INACTIVE INGREDIENT

AQUA

Propylene Glycol

Glycerin

CARBOMER

AMINOMETHYL PROPANOL

INDICATIONS AND USAGE

apply approptiate amount of this product to The palm.rub with both hands until dry without washing.

ACTIVE INGREDIENT

ALCOHOL

keep out of reach of children

PURPOSE

Disinfection
Sterilization

WARNINGS

1 keep out of reach of children.cont be swallowed just for External disinfectant.
2.Avoid to use together with agonist drugs.
3.Use in coution if allegric.
4.Flammable liquid.keep product away from heal.
5.Store in a cool dry place.
6.Always seals after use before Validity period.